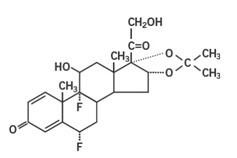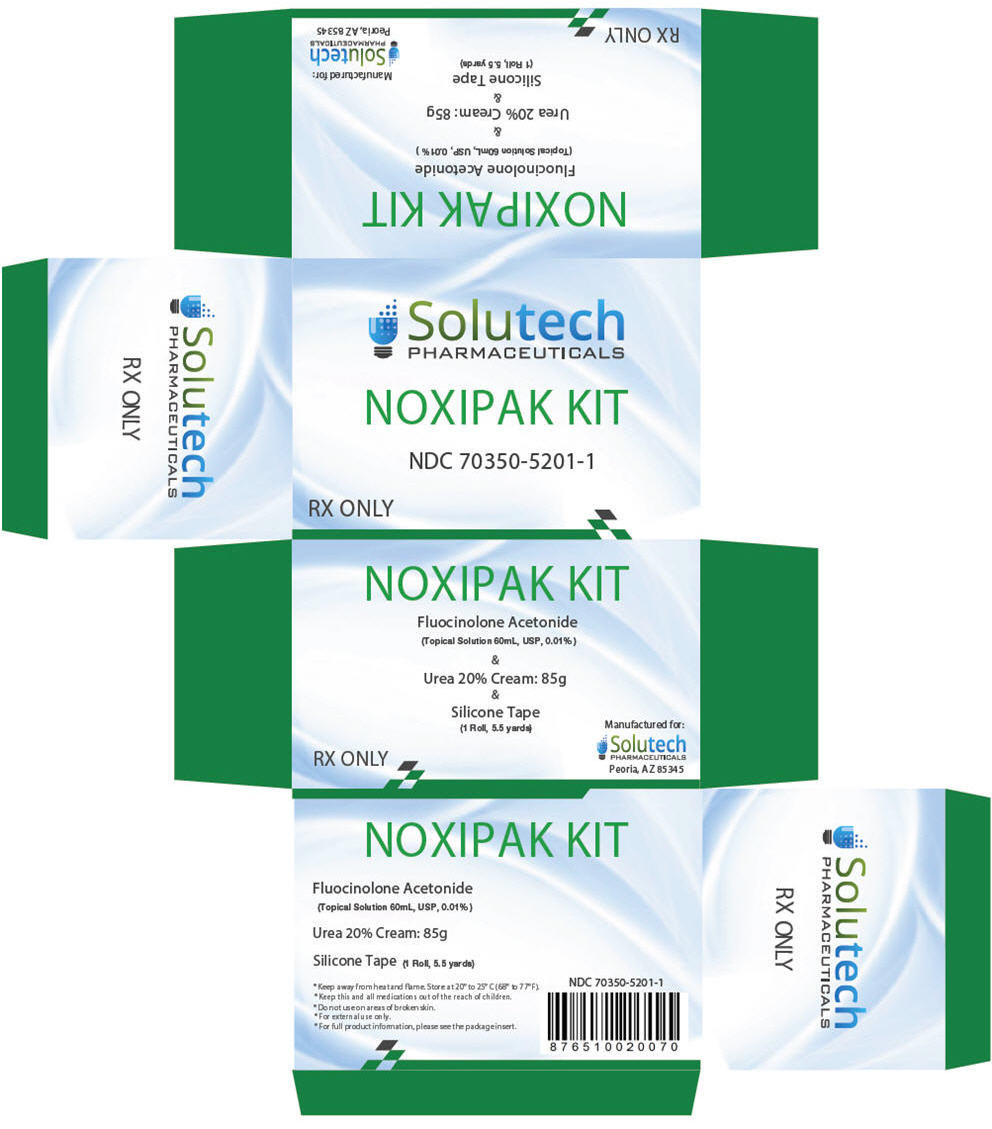 DRUG LABEL: NOXIPAK
NDC: 70350-5201 | Form: KIT | Route: TOPICAL
Manufacturer: SOLUTECH PHARMACEUTICALS LLC
Category: prescription | Type: HUMAN PRESCRIPTION DRUG LABEL
Date: 20171108

ACTIVE INGREDIENTS: FLUOCINOLONE ACETONIDE 0.1 mg/1 mL; UREA 17 g/85 g
INACTIVE INGREDIENTS: ANHYDROUS CITRIC ACID; PROPYLENE GLYCOL; CARBOXYPOLYMETHYLENE; ISOPROPYL PALMITATE; ISOPROPYL MYRISTATE; PROPYLENE GLYCOL; WATER; SODIUM LAURETH-3 SULFATE; STEARIC ACID; TROLAMINE; XANTHAN GUM

NOXIPAK KIT

(NDC 70350-5201-1)

For external use only.
Not for ophthalmic use.

Rx Only

NOXIPAK KIT DESCRIPTION

NOXIPAK is supplied as 3 components in a kit:

- FLUOCINOLONE ACETONIDE TOPICAL SOLUTION USP, 0.01% (NDC 52565-012-59), 60mL
- UREA 20% CREAM, 85g (NDC 58980-610-30), 85g
- SILICONE TAPE, 1 Roll, 5.5 Yards

INDICATION AND USAGE

For the management of hypertrophic tissues, keloid tissues, dermatitis and dermatoses. [This statement has not been evaluated by the FDA. This product is not intended to diagnose, treat, cure, or prevent disease.]

DOSAGE AND ADMINISTRATION

First apply Fluocinolone Acetonide 0.01% Topical Solution to the affected area, rub into skin until absorbed. Then apply Urea 20% cream and rub into skin until completely absorbed. Apply twice a day or as directed by your physician. Cover the affected area with silicone tape at bedtime or as directed by your physician.

WARNINGS

FOR EXTERNAL USE ONLY. Avoid contact with eyes, lips or mucous membranes. Do not use on areas of broken skin.

CONTRAINDICATIONS

Do not use if known hypersensitivity to any of the listed ingredients of any of the components included on the kit.

PRECAUTIONS

Stop use and ask a doctor if redness or irritation develops. Keep this and all other medications out of the reach of children. If swallowed, get medical help or contact a Poison Control Center right away.

PREGNANCY

If pregnant or breast feeding, ask a health professional before use.

HOW SUPPLIED

STORAGE AND HANDLING

Store at 20°-25°C (68° to 77°F); Keep away from heat and flame. Protect from freezing. [See USP Controlled Room Temperature.]

MANUFACTURED FOR:
SOLUTECH PHARMACEUTICALS LLC
PEORIA, AZ 85345

Rx Only

Fluocinolone Acetonide Topical Solution USP, 0.01%

Rx Only

DESCRIPTION

Fluocinolone Acetonide Topical Solution USP, 0.01% is intended for topical administration. The active component is the corticosteroid fluocinolone acetonide, which has the chemical name pregna-1,4-diene-3,20-dione,6,9-difluoro-11,21-dihydroxy16,17[(methylethylidene)bis(oxy)]-, (6α,11β,16α)-. It has the following chemical structure:

Fluocinolone Acetonide Solution USP contains fluocinolone acetonide 0.1 mg/mL in a water-washable base of citric acid and propylene glycol.

CLINICAL PHARMACOLOGY

Topical corticosteroids share anti-inflammatory, antipruritic and vasoconstrictive actions.

The mechanism of anti-inflammatory activity of the topical corticosteroids is unclear. Various laboratory methods, including vasoconstrictor assays, are used to compare and predict potencies and/or clinical efficacies of the topical corticosteroids. There is some evidence to suggest that a recognizable correlation exists between vasoconstrictor potency and therapeutic efficacy in man.

Pharmacokinetics

The extent of percutaneous absorption of topical corticosteroids is determined by many factors including the vehicle, the integrity of the epidermal barrier, and the use of occlusive dressings.

Topical corticosteroids can be absorbed from normal intact skin. Inflammation and/or other diseaseprocesses in the skin increase the percutaneous absorption. Occlusive dressings substantially increase the percutaneous absorption of topical corticosteroids. Thus, occlusive dressings may be a valuable therapeutic adjunct for treatment of resistant dermatoses (See DOSAGE AND ADMINISTRATION).

Once absorbed through the skin, topical corticosteroids are handled through pharmacokinetic pathways similar to systemically administered corticosteroids. Corticosteroids are bound to plasma proteins in varying degrees. Corticosteroids are metabolized primarily in the liver and are then excreted by the kidneys. Some of the topical corticosteroids and their metabolites are also excreted into the bile.

INDICATIONS AND USAGE

Fluocinolone Acetonide Topical Solution is indicated for the relief of the inflammatory and pruritic manifestations of corticosteroid-responsive dermatoses.

CONTRAINDICATIONS

Topical corticosteroids are contraindicated in those patients with a history of hypersensitivity to any of components of the preparation.

PRECAUTIONS

General

Systemic absorption of topical corticosteroids has produced reversible hypothalamic-pituitary-adrenal (HPA) axis suppression, manifestations of Cushing's syndrome, hyperglycemia, and glycosuria in some patients.

Conditions which augment systemic absorption include the application of the more potent steroids, use over large surface areas, prolonged use, and the addition of occlusive dressings.

Therefore, patients receiving a large dose of a potent topical steroid applied to a large surface area or under an occlusive dressing should be evaluated periodically for evidence of HPA axis suppression by using the urinary free cortisol and ACTH stimulation tests. If HPA axis suppression is noted, an attempt should be made to withdraw the drug, to reduce the frequency of application, or to substitute a less potent steroid.

Recovery of HPA axis function is generally prompt and complete upon discontinuation of the drug. Infrequently, signs and symptoms of steroid withdrawal may occur, requiring supplemental systemic corticosteroids.

Children may absorb proportionally larger amounts of topical-corticosteroids and thus be more susceptible to systemic toxicity (See PRECAUTIONS – Pediatric Use).

If irritation develops, topical corticosteroids should be discontinued and appropriate therapy instituted.

As with any topical corticosteroid product, prolonged use may produce atrophy of the skin and subcutaneous tissues. When used on intertriginous or flexor areas, or on the face, this may occur even with short-term use.

In the presence of dermatological infections, the use of an appropriate antifungal or antibacterial agent should be instituted. If a favorable response does not occur promptly, the corticosteroid should be discontinued until the infection has been adequately controlled.

Information for the Patient

Patients using topical corticosteroids should receive the following information and instructions:

1. This medication is to be used as directed by the physician. It is for external use only. Avoid contact with the eyes.
2. Patients should be advised not to use this medication for any disorder other than for which it was prescribed.
3. The treated skin area should not be bandaged or otherwise covered or wrapped so as to be occlusive unless directed by the physician.
4. Patients should report any signs of local adverse reactions especially under occlusive dressing.
5. Parents of pediatric patients should be advised not to use tight-fitting diapers or plastic pants on a child being treated in the diaper area, as these garments may constitute occlusive dressings.

Laboratory Tests

The following tests may be helpful in evaluating HPA axis suppression:

Urinary free cortisol test
ACTH stimulation test

Carcinogenesis, Mutagenesis and Impairment of Fertility

Long-term animal studies have not been performed to evaluate the carcinogenic potential or the effect on fertility of topical corticosteroids.

Studies to determine mutagenicity with prednisolone and hydrocortisone have revealed negative results.

Pregnancy Category C

Corticosteroids are generally teratogenic in laboratory animals when administered systemically at relatively low dosage levels. The more potent corticosteroids have been shown to be teratogenic after dermal application in laboratory animals. There are no adequate and well controlled studies in pregnant women on teratogenic effects from topically applied corticosteroids. Therefore, topical corticosteroids should be used during pregnancy only if the potential benefit justifies the potential risk to the fetus. Drugs of this class should not be used extensively on pregnant patients, in large amounts, or for prolonged periods of time.

Nursing Mothers

It is not known whether topical administration of corticosteroids could result in sufficient systemic absorption to produce detectable quantities in breast milk. Systemically administered corticosteroids are secreted into breast milk in quantities not likely to have a deleterious effect on the infant. Nevertheless, caution should be exercised when topical corticosteroids are administered to a nursing woman.

Pediatric Use

Pediatric patients may demonstrate greater susceptibility to topical corticosteroid-induced HPA axis suppression and Cushing's syndrome than mature patients because of a larger skin surface area to body weight ratio.

Hypothalamic-pituitary-adrenal (HPA) axis suppression, Cushing's syndrome, and intracranial hypertension have been reported in children receiving topical corticosteroids. Manifestations of adrenal suppression in children include linear growth retardation, delayed weight gain, low plasma cortisol levels, and absence of response to ACTH stimulation. Manifestations of intracranial hypertension include bulging fontanelles, headaches, and bilateral papilledema.

Administration of topical corticosteroids to children should be limited to the least amount compatible with an effective therapeutic regimen. Chronic corticosteroid therapy may interfere with the growth and development of children.

ADVERSE REACTIONS

The following local adverse reactions are reported infrequently with topical corticosteroids, but may occur more frequently with the use of occlusive dressings. These reactions are listed in an approximate decreasing order of occurrence:

Burning
Itching
Irritation
Dryness
Folliculitis
Hypertrichosis
Acneiform eruptions
Hypopigmentation

Perioral dermatitis
Allergic contact dermatitis
Maceration of the skin
Secondary infection
Skin atrophy
Striae
Miliaria

OVERDOSAGE

Topically applied corticosteroids can be absorbed in sufficient amounts to produce systemic effects (See PRECAUTIONS).

DOSAGE AND ADMINISTRATION

Fluocinolone Acetonide Topical Solution is generally applied to the affected area as a thin film from two to four times daily depending on the severity of the condition. In hairy sites, the hair should be parted to allow direct contact with the lesion.

Occlusive dressing may be used for the management of psoriasis or recalcitrant conditions.

If an infection develops, the use of occlusive dressings should be discontinued and appropriate antimicrobial therapy instituted.

HOW SUPPLIED

Fluocinolone Acetonide Topical Solution 0.01%:
60 mL bottle with applicator tip - NDC 52565-012-59

STORAGE

Store at room temperature 15° to 25°C (59° to 77°F); avoid freezing and excessive heat above 40°C (104°F).

Teligent Pharma, Inc.
Buena, New Jersey 08310

PI012
Iss. 11/12

UREA 20% CREAM

Drug Description

Active Ingredient

Urea 20%

Purpose

Keratolytic

Inactive Ingredients

Carbomer, Fragrance, Isopropyl Myristate, Isopropyl Palmitate, Propylene Glycol, Purified Water, Sodium Laureth Sulfate, Stearic Acid, Trolamine and Xanthan Gum.

Warnings

DO NOT USE

FOR EXTERNAL USE ONLY. Avoid contact with eyes, lips or mucous membranes. Do not use on areas of broken skin. Do not use if known hypersensitivity to any of the listed ingredients.

Precautions

Stop use and ask a doctor if redness or irritation develops. Keep this and all other medications out of reach of children. If swallowed, get medical help or contact a Poison Control Center right away.

Pregnancy

If pregnant or breast feeding, ask a health professional before use.

Directions

Apply to the affected areas twice a day or as directed by a physician. Rub into the skin until completely absorbed.

STORAGE AND HANDLING

Store at controlled room temperature 15° - 30°C (59° - 86°F). Protect from Freezing. See Crimp and end of carton for Lot Number and Expiration Date.

UC20(3)-200907

Description

Silicone tape is a silicone blended tape. This tape is designed to not harm the skin when it is being removed. Most tapes pull the skin and the small hairs, causing unnecessary damage. This Silicone tape has a paper blended backing that allows a gentle, but strong adhesion to the skin that remains constant. Most tapes increase their adhesion over time, which increases the damage when they are removed.

The silicone tape can be re-positioned without losing any of its tacky qualities. The gentle adhesion does not lower the quality of the hold either. This tape is adhesive enough that it can be worn in the shower without losing effectiveness.

Purpose

For alleviating tension on the scar and its surrounding skin. Tension on a wound and scar is known to increase scar tissue formation.

Because of its adherence, silicone tape reduces tension (e.g. tear and stretch) along the incision line or wound which is known to minimize the degree of scarring in terms of spreading or thickening.

Warnings

FOR EXTERNAL USE ONLY. Avoid contact with eyes, lips or mucous membranes. Do not use on areas of broken skin. Do not use if you have known hypersensitivity to silicone

Precautions

Stop use and ask a doctor if redness or irritation or rash develops. Keep out of reach of children.

Directions

Apply to the affected area as directed by your physician.

PRINCIPAL DISPLAY PANEL - Kit Carton

Solutech
PHARMACEUTICALS

NOXIPAK KIT

NDC 70350-5201-1

RX ONLY